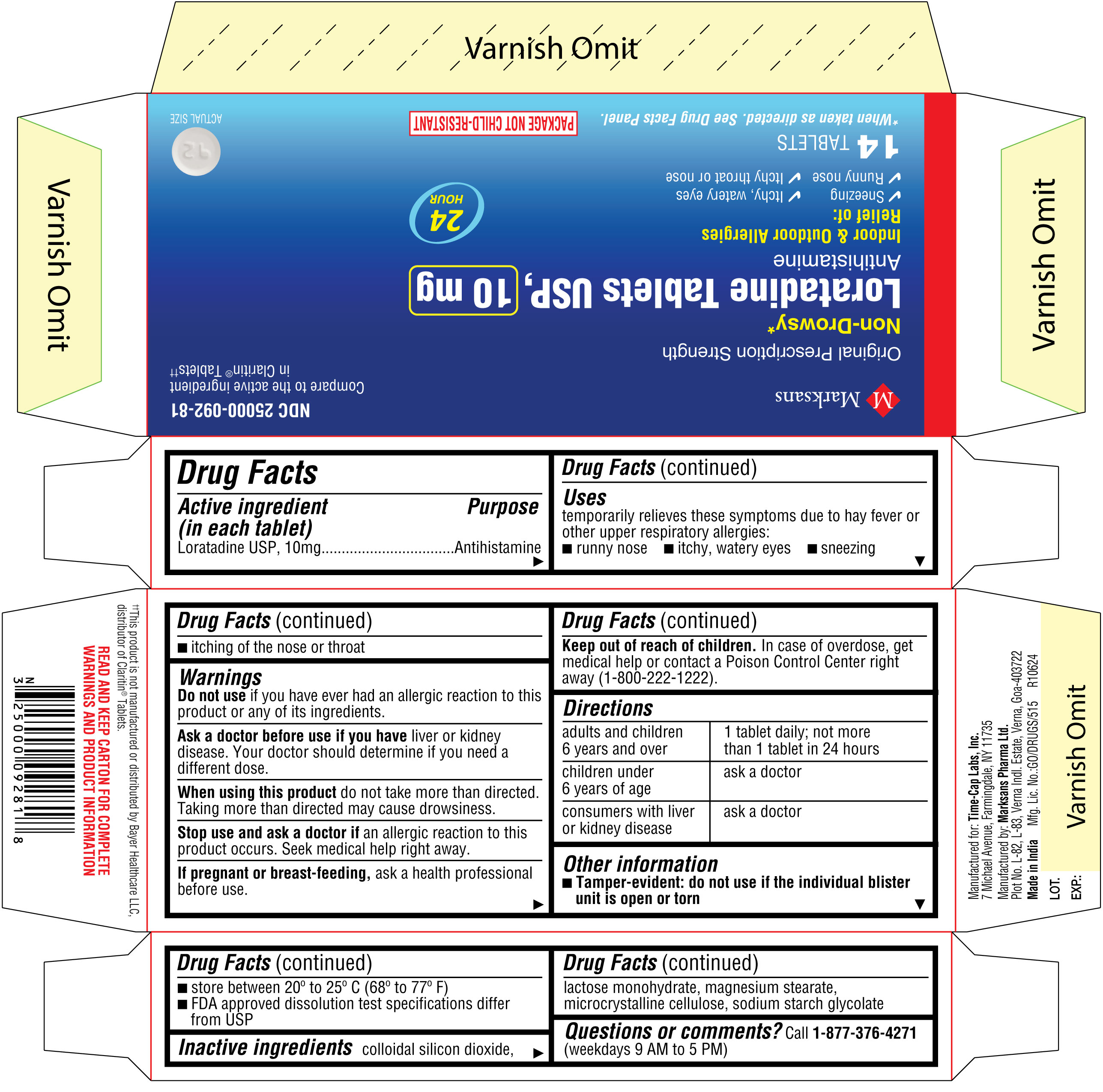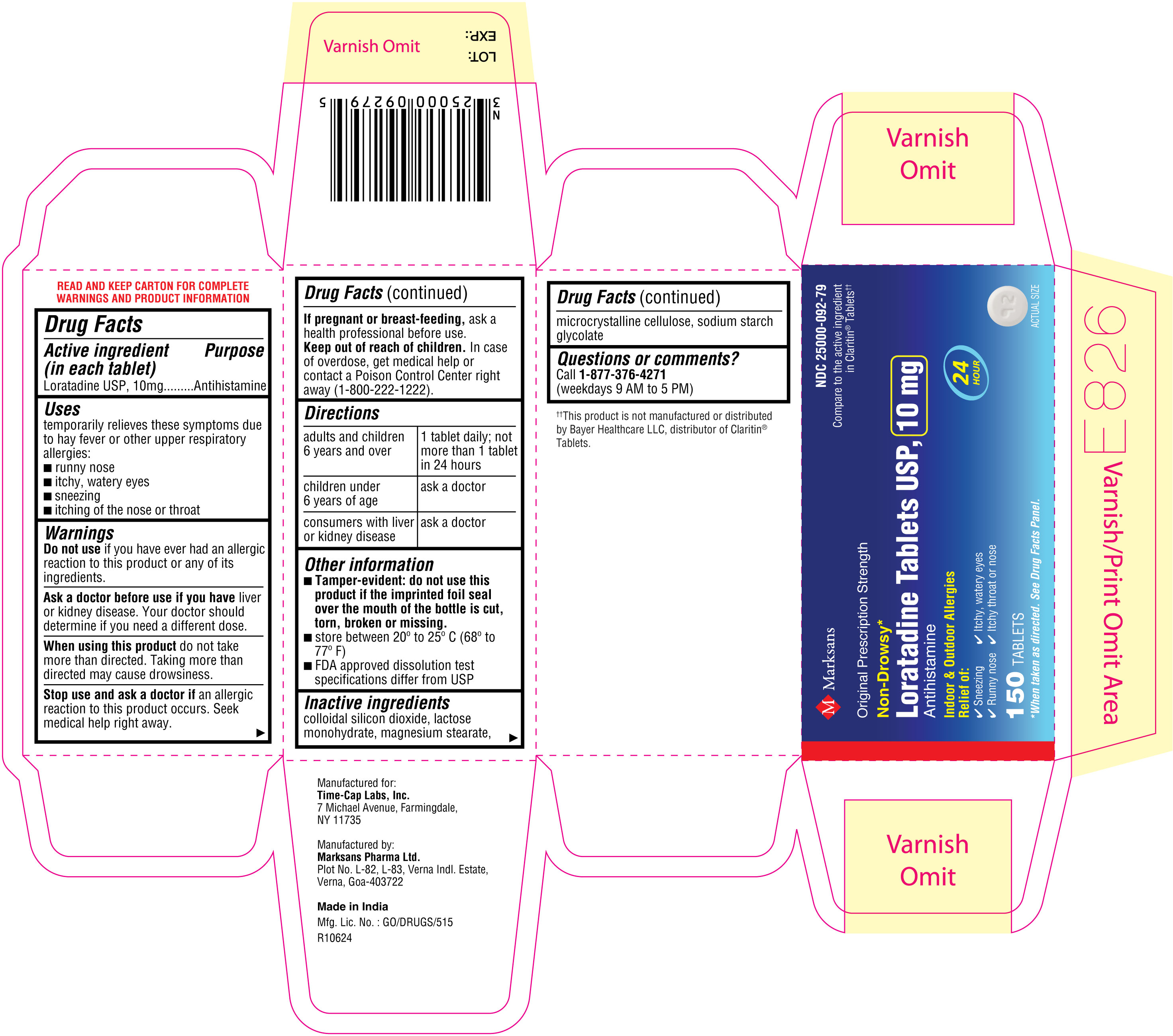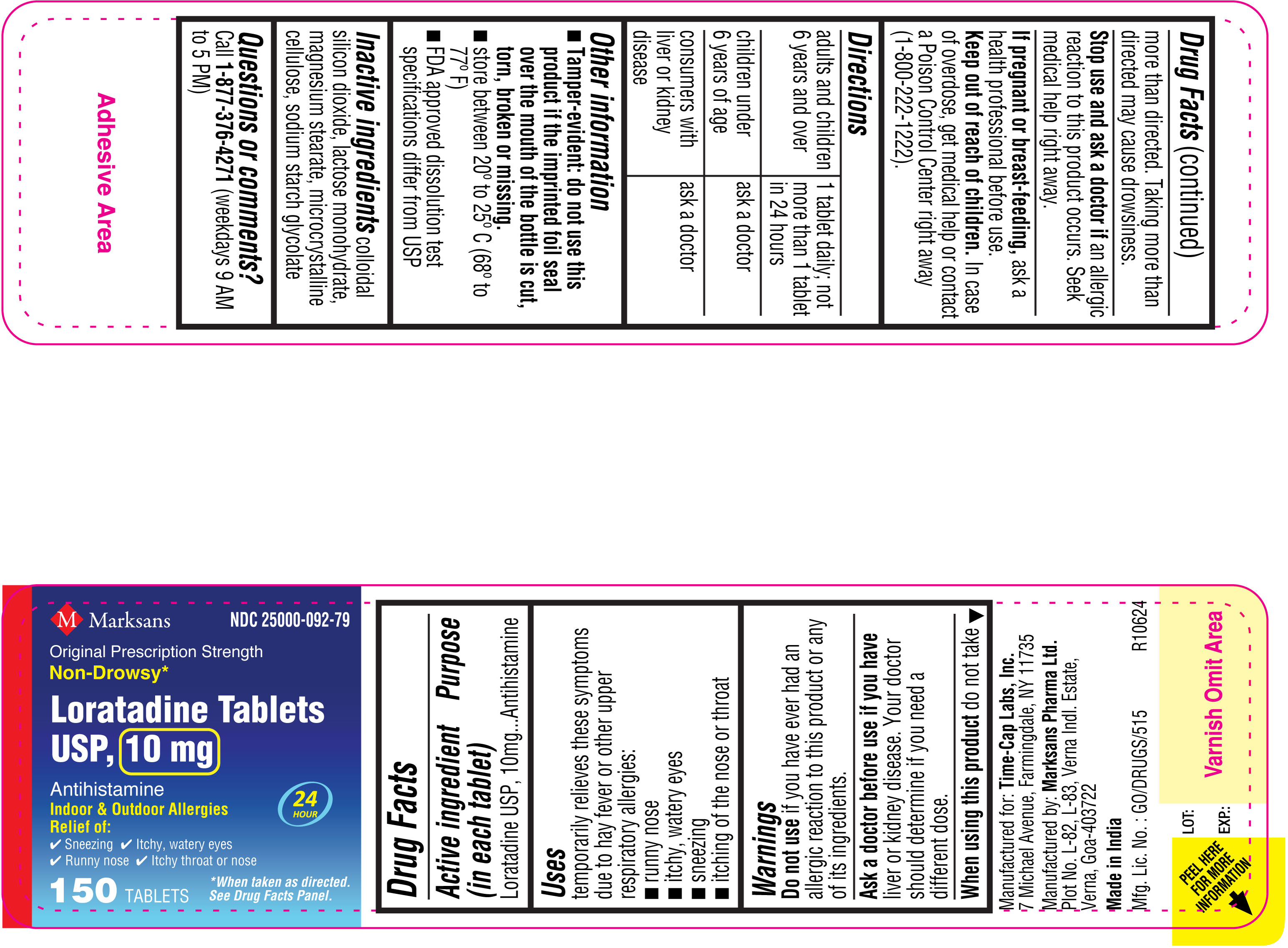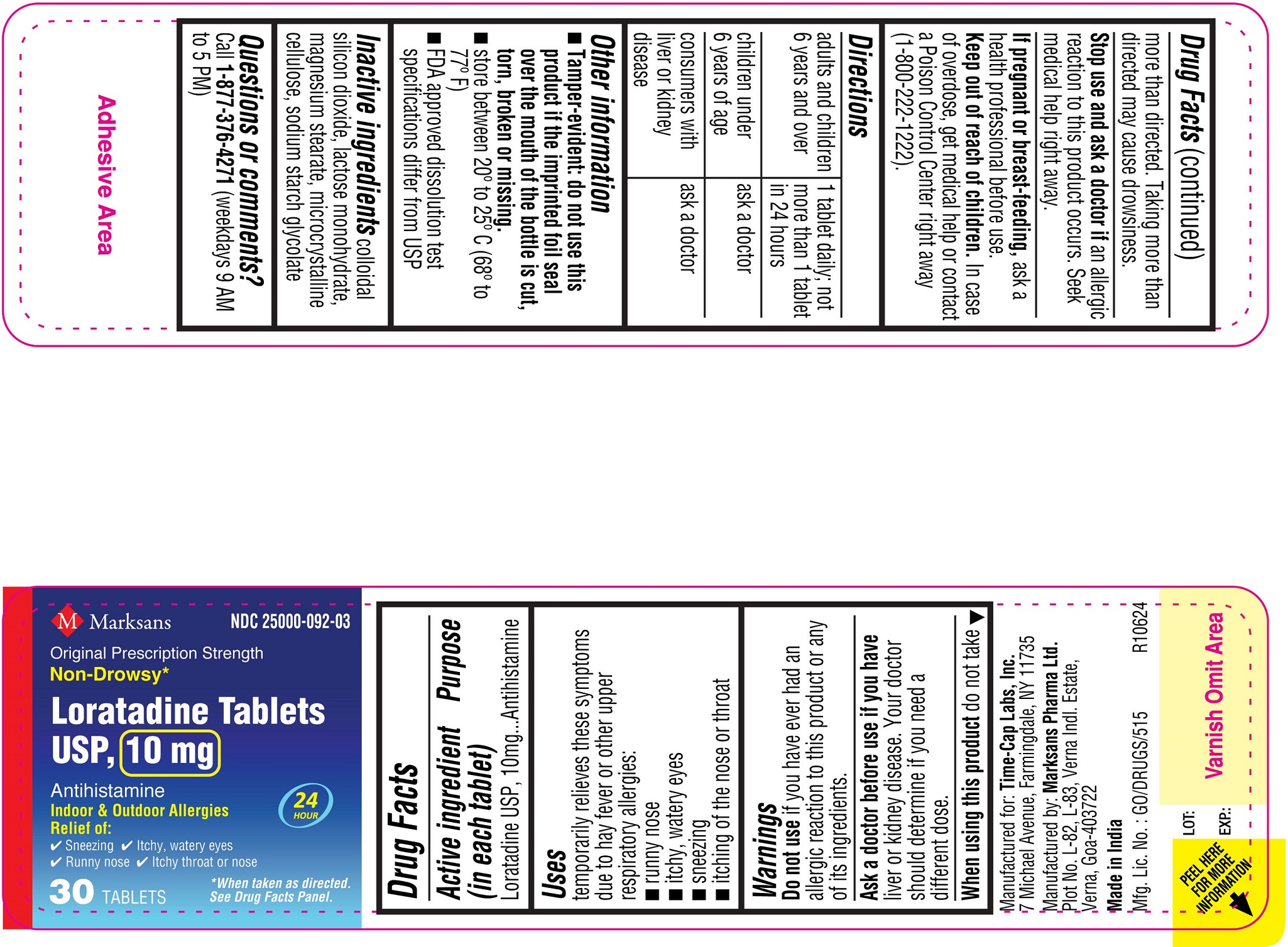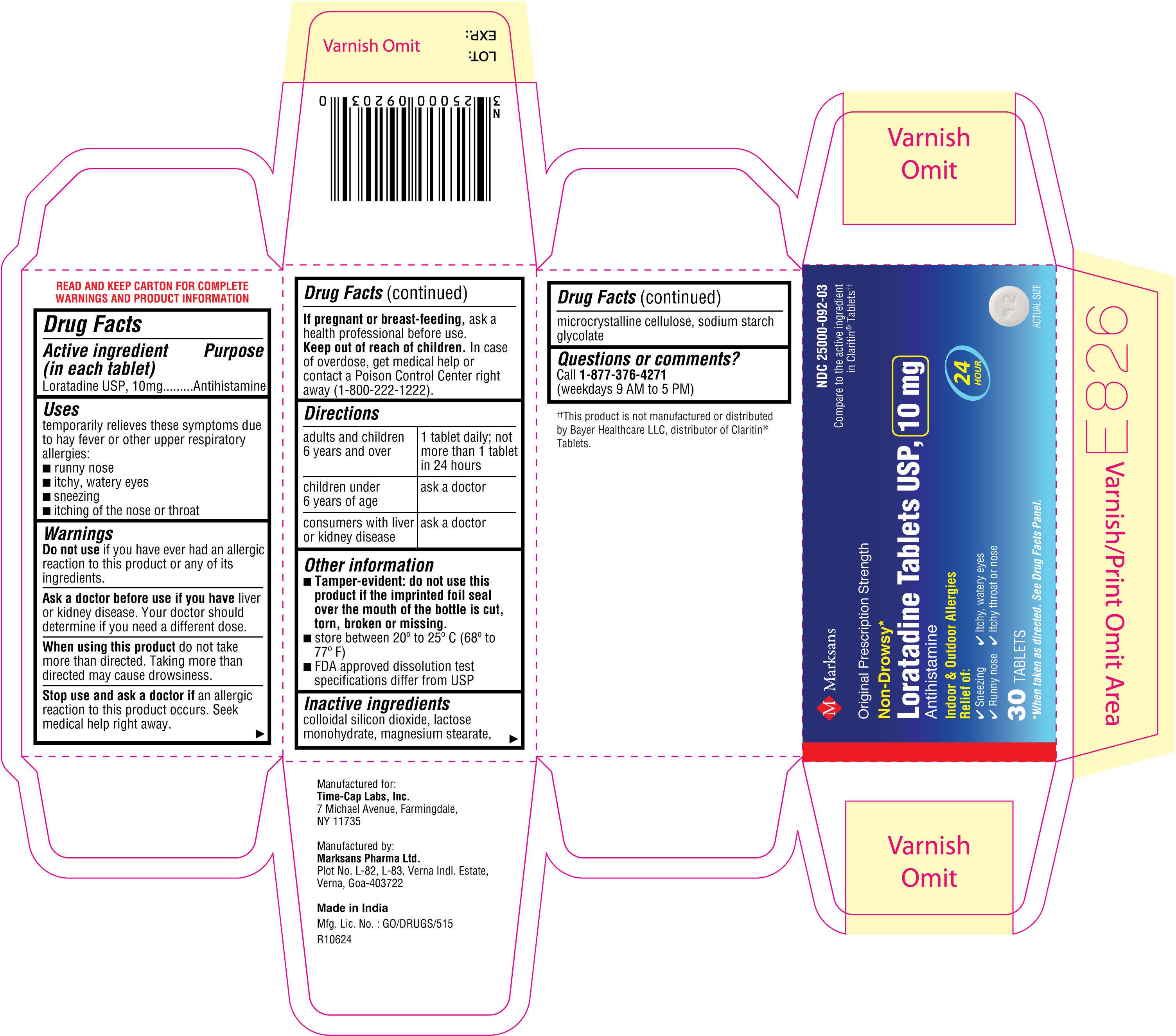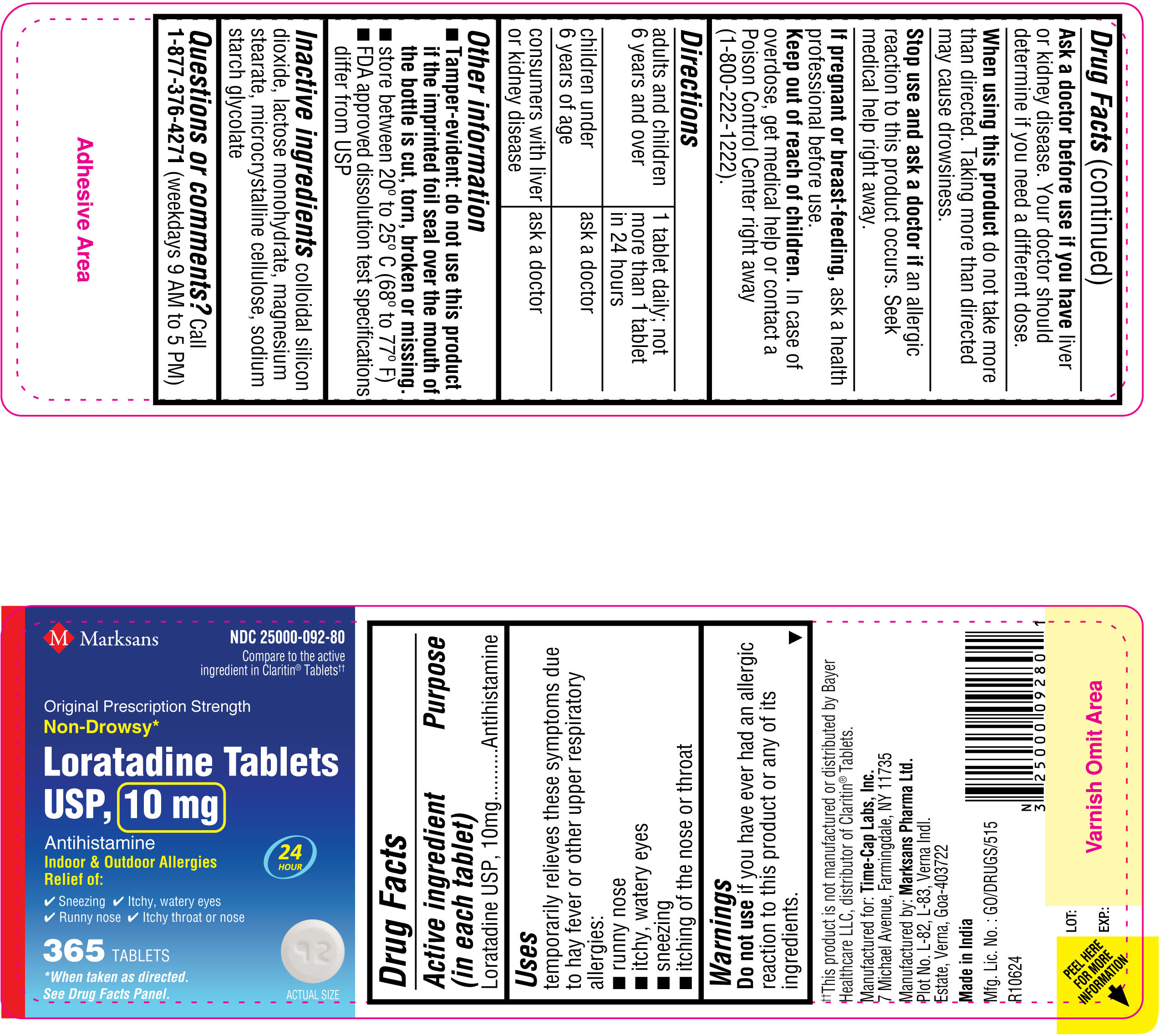 DRUG LABEL: Loratadine 10mg
NDC: 25000-092 | Form: TABLET
Manufacturer: MARKSANS PHARMA LIMITED
Category: otc | Type: Human OTC Drug Label
Date: 20241125

ACTIVE INGREDIENTS: LORATADINE 10 mg/1 1
INACTIVE INGREDIENTS: SILICON DIOXIDE; LACTOSE MONOHYDRATE; MAGNESIUM STEARATE; MICROCRYSTALLINE CELLULOSE 101; SODIUM STARCH GLYCOLATE TYPE A

Loratadine Tablets USP 10mg

ACTIVE INGREDIENT(S)

Active ingredient (in each tablet)
Loratadine USP, 10 mg

PURPOSE

Antihistamine

USE(S)

Uses
temporarily relieves these symptoms due to hay fever or other upper respiratory allergies:

- runny nose
- itchy, watery eyes
- sneezing
- itching of the nose or throat

WARNINGS

Do not use if you have ever had an allergic reaction to this product or any of its ingredients.

Ask a doctor before use if you have liver or kidney disease. Your doctor should determine if you need a different dose.

When using this product do not take more than directed. Taking more than directed may cause drowsiness.

STOP USE AND ASK DOCTOR IF

Stop use and ask a doctor if an allergic reaction to this product occurs. Seek medical help right away.

PREGNANCY/BREASTFEEDING

If pregnant or breast-feeding, ask a health professional before use.

Keep out of reach of children. In case of overdose, get medical help or contact a Poison Control Center right away (1-800-222-1222).

DIRECTIONS

adults and children 6 years and over | 1 tablet daily; not more than 1 tablet in 24 hours
children under 6 years of age | ask a doctor
consumers with liver or kidney disease | ask a doctor

OTHER REQUIRED WARNINGS

Other information

- For Bottle pack: Tamper-evident: do not use this product if the imprinted foil seal over the mouth of the bottle is cut, torn, broken or missing.
- For Blister pack: Tamper-evident: do not use if the individual blister unit is open or torn
- store between 20º to 25º C (68º to 77º F)
- FDA approved dissolution test specifications differ from USP

Inactive ingredients

Inactive ingredients colloidal silicon dioxide, lactose monohydrate, magnesium stearate, microcrystalline cellulose, sodium starch glycolate

Questions or comments? Call 1-877-376-4271 (weekdays 9 AM to 5 PM)
Manufactured for:
Time-Cap Labs, Inc.
7 Michael Avenue,
Farmingdale,
NY 11735
Manufactured by:
Marksans Pharma Ltd.
Plot No. L-82, L-83
Verna Indl. Estate
Verna, Goa-403722
Made in India

PRINCIPAL DISPLAY PANEL

NDC: 25000-092-81
Loratadine Tablets USP, 10 mg
14's count Carton

NDC: 25000-092-03
Loratadine Tablets USP, 10 mg
30's count Carton

NDC: 25000-092-03
Loratadine Tablets USP, 10 mg
30's count Label

NDC: 25000-092-79
Loratadine Tablets USP, 10 mg
150's count Carton

NDC: 25000-092-79
Loratadine Tablets USP, 10 mg
150's count Label

NDC: 25000-092-80
Loratadine Tablets USP, 10 mg
365's count Label